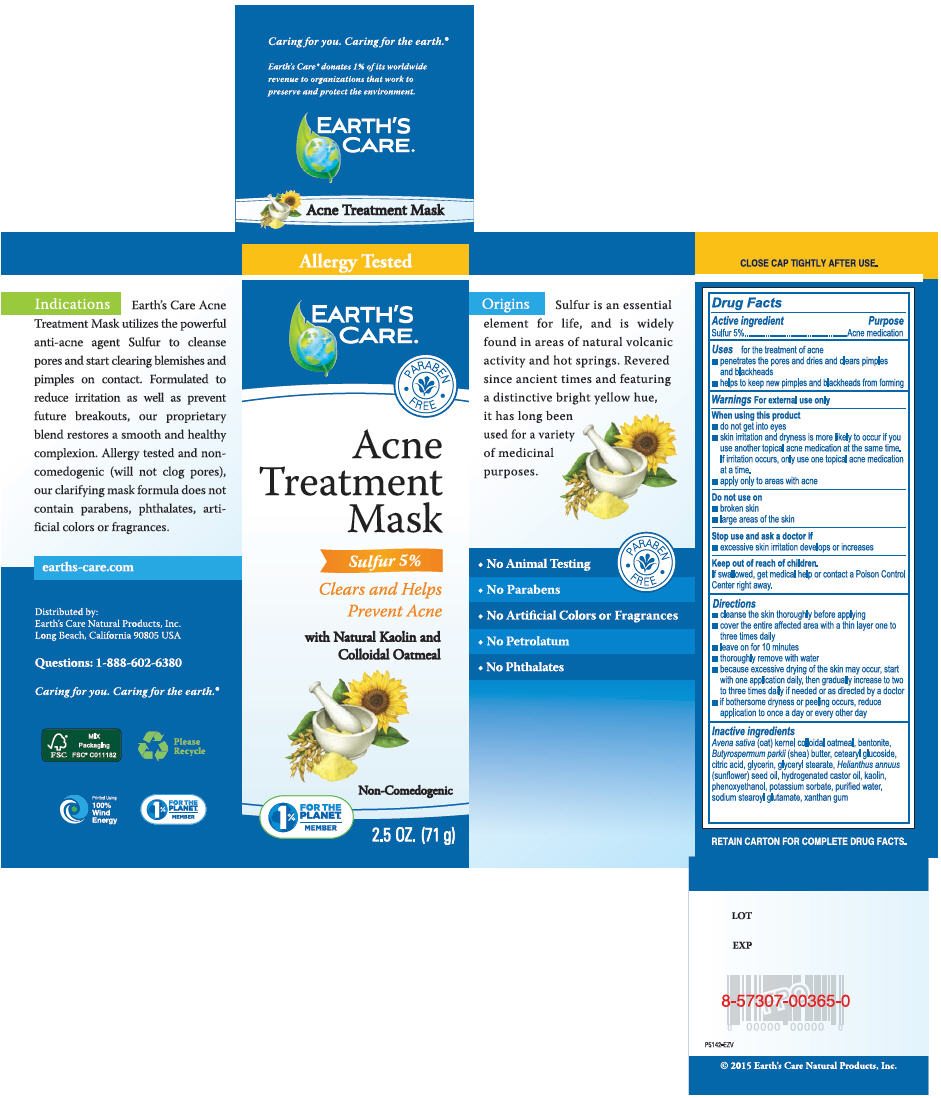 DRUG LABEL: Earths Care Acne Treatment Mask
NDC: 24286-1556 | Form: CREAM
Manufacturer: DLC Laboratories, Inc.
Category: otc | Type: HUMAN OTC DRUG LABEL
Date: 20260107

ACTIVE INGREDIENTS: SULFUR 5 g/100 g
INACTIVE INGREDIENTS: OATMEAL; BENTONITE; SHEA BUTTER; CETEARYL GLUCOSIDE; CITRIC ACID MONOHYDRATE; GLYCERIN; GLYCERYL MONOSTEARATE; SUNFLOWER OIL; HYDROGENATED CASTOR OIL; KAOLIN; PHENOXYETHANOL; POTASSIUM SORBATE; WATER; SODIUM STEAROYL GLUTAMATE; XANTHAN GUM

Earths Care Acne Treatment Mask

Active ingredients

Sulfur 5%

Purpose

Acne medication

Uses

for the treatment of acne

- penetrates the pores and dries and clears pimples and blackheads
- helps to keep new pimples and black heads from forming.

Warnings

For external use only

When using this product

- do not get into eyes
- skin irritation and dryness is more likely to occur if you use another topical acne medication at the same time. If irritation occurs only use one topical acne medication at a time.
- apply only to areas with acne.

Do not use on

- broken skin
- large areas of the skin

Stop use and ask a doctor if

- excessive skin irritation develops or increases

Keep out of reach of children.

If swallowed, get medical help or contact a Poison Control Center right away.

Directions

- cleanse the skin thoroughly before applying
- cover the entire affected area with a thin layer one to three times daily
- leave on for 10 minutes
- thoroughly remove with water
- because excessive during of the skin may occur, start with one application daily, then gradually increase to two to three times daily if needed or as directed by a doctor
- if bothersome dryness or peeling occurs, reduce application to once a day or every other day

Inactive ingredients

Avena sativa (oat) kernel colloidal oatmeal, bentonite, Butyrospermum parkii (shea) butter, cetearyl glucoside, citric acid, glycerin, glyceryl stearate, Helianthus annuus (sunflower) seed oil, hydrogenated castor oil, kaolin, phenoxyethanol, potassium sorbate, purified water, sodium stearoyl glutamate, xanthan gum.

Indications

Earth's Care Acne Treatment Mask utilizes the powerful anti-acne agent Sulfur to cleanse pores and start clearing blemishes and pimples on contact. Formulated to reduce irritation as well as prevent future breakouts, our proprietary blend restores a smooth and healthy complexion. Allergy tested and non-comedogenic (will not clog pores), our clarifying mask formula does not contain parabens, phthalates, artificial colors or fragrance.

earths-care.com

* Allergy Tested for allergy

Distributed by:

Earth's Care Natural Products, Inc.
Long Beach, California 90805 USA

Questions: 1-888-602-6380

Caring for you.
Caring for the earth.

Earth's Care donates 1% of its worldwide revenue to organizations that work to preserve and protect the environment. EARTH'S CARE. Acne Spot Treatment

Origins Sulfur is an essential element for life, and is widely found in areas of natural volcanic activity and hot springs. Revered since ancient times and featuring a distinctive bright yellow hue, it has long been used for a variety of medicinal purposes. ALLERGY TESTED.

* No Animal Testing
* No Parabens
* No Artificial Colors or Fragrances
* No Petrolatum
* No Phthalates

PRINCIPAL DISPLAY PANEL - 71 g Tube Box

Allergy Tested

EARTH'S
CARE ®

PARABEN
FREE

Acne
Treatment
Mask

Sulfur 5%

Clears and Helps
Prevent Acne

with Natural Kaolin and
Colloidal Oatmeal

Non-Comedogenic

1%
FOR THE
PLANET℠
MEMBER

2.5 OZ. (71 g)